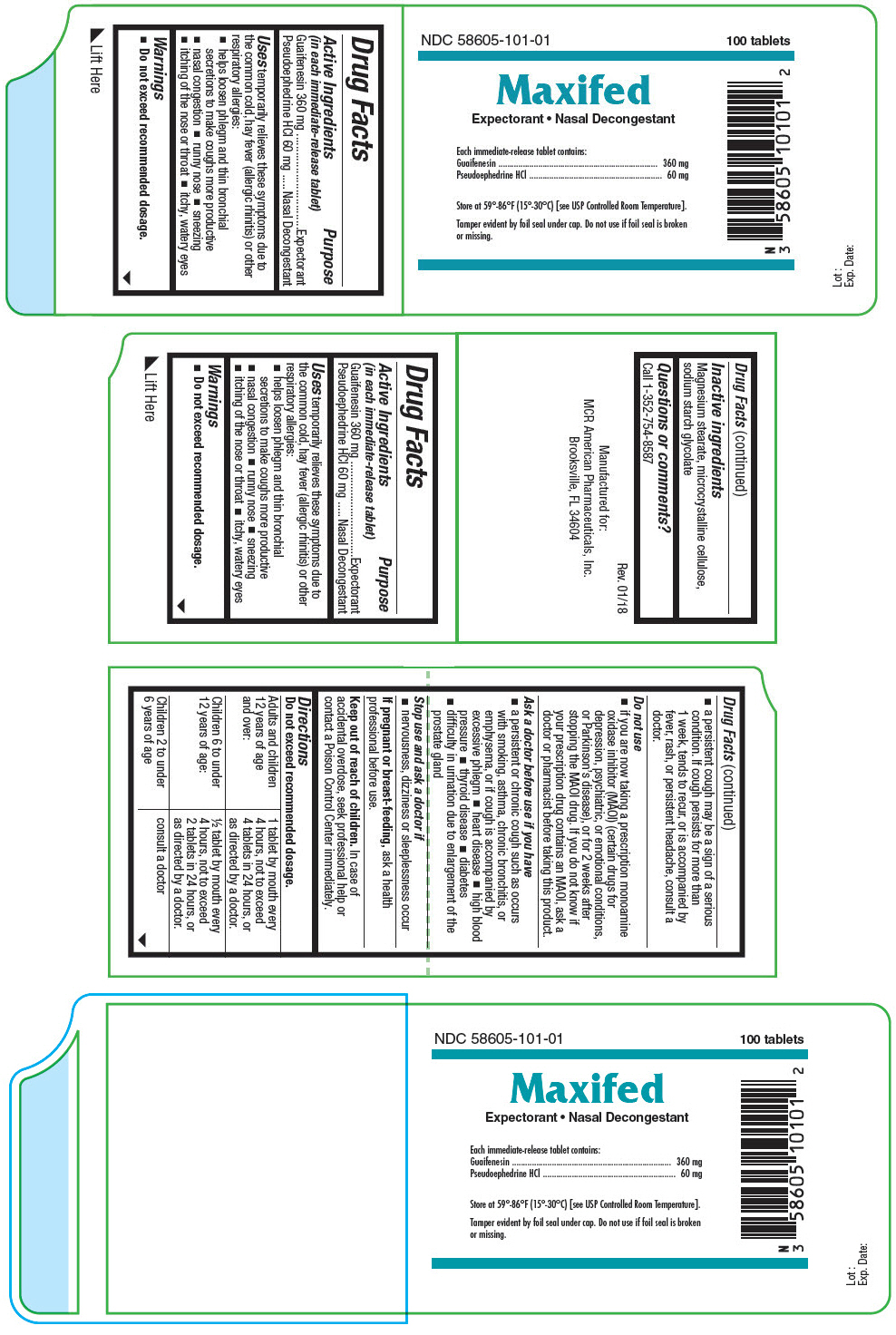 DRUG LABEL: Maxifed
NDC: 58605-101 | Form: TABLET
Manufacturer: MCR American Pharmaceuticals, Inc.
Category: otc | Type: HUMAN OTC DRUG LABEL
Date: 20180315

ACTIVE INGREDIENTS: GUAIFENESIN 360 mg/1 1; Pseudoephedrine Hydrochloride 60 mg/1 1
INACTIVE INGREDIENTS: Magnesium Stearate; Microcrystalline Cellulose; SODIUM STARCH GLYCOLATE TYPE A POTATO

Maxifed

Drug Facts

ACTIVE INGREDIENT

Active Ingredients (in each immediate-release tablet) | Purpose
Guaifenesin 360 mg | Expectorant
Pseudoephedrine HCl 60 mg | Nasal Decongestant

Uses

temporarily relieves these symptoms due to the common cold, hay fever (allergic rhinitis) or other respiratory allergies:

- helps loosen phlegm and thin bronchial secretions to make coughs more productive
- nasal congestion
- runny nose
- sneezing
- itching of the nose or throat
- itchy, watery eyes

Warnings

- Do not exceed recommended dosage.
- a persistent cough may be a sign of a serious condition. If cough persists for more than 1 week, tends to recur, or is accompanied by fever, rash, or persistent headache, consult a doctor.

Do not use

- if you are now taking a prescription monoamine oxidase inhibitor (MAOI) (certain drugs for depression, psychiatric, or emotional conditions, or Parkinson's disease), or for 2 weeks after stopping the MAOI drug. If you do not know if your prescription drug contains an MAOI, ask a doctor or pharmacist before taking this product.

Ask a doctor before use if you have

- a persistent or chronic cough such as occurs with smoking, asthma, chronic bronchitis, or emphysema, or if cough is accompanied by excessive phlegm
- heart disease
- high blood pressure
- thyroid disease
- diabetes
- difficulty in urination due to enlargement of the prostate gland

Stop use and ask a doctor if

- nervousness, dizziness or sleeplessness occur

PREGNANCY OR BREAST FEEDING

If pregnant or breast-feeding, ask a health professional before use.

Keep out of reach of children. In case of accidental overdose, seek professional help or contact a Poison Control Center immediately.

Directions

Do not exceed recommended dosage.

Adults and children 12 years of age and over: | 1 tablet by mouth every 4 hours, not to exceed 4 tablets in 24 hours, or as directed by a doctor.
Children 6 to under 12 years of age: | ½ tablet by mouth every 4 hours, not to exceed 2 tablets in 24 hours, or as directed by a doctor.
Children 2 to under 6 years of age | consult a doctor

Inactive ingredients

Magnesium stearate, microcrystalline cellulose, sodium starch glycolate

Questions or comments?

Call 1-352-754-8587

PRINCIPAL DISPLAY PANEL - 360 mg/60 mg Tablet Bottle Label

NDC 58605-101-01
100 tablets

Maxifed

Expectorant • Nasal Decongestant

Each immediate-release tablet contains:
Guaifenesin 360 mg
Pseudoephedrine HCl 60 mg

Store at 59°-86°F (15°-30°C) [see USP Controlled Room Temperature].

Tamper evident by foil seal under cap. Do not use if foil seal is broken
or missing.